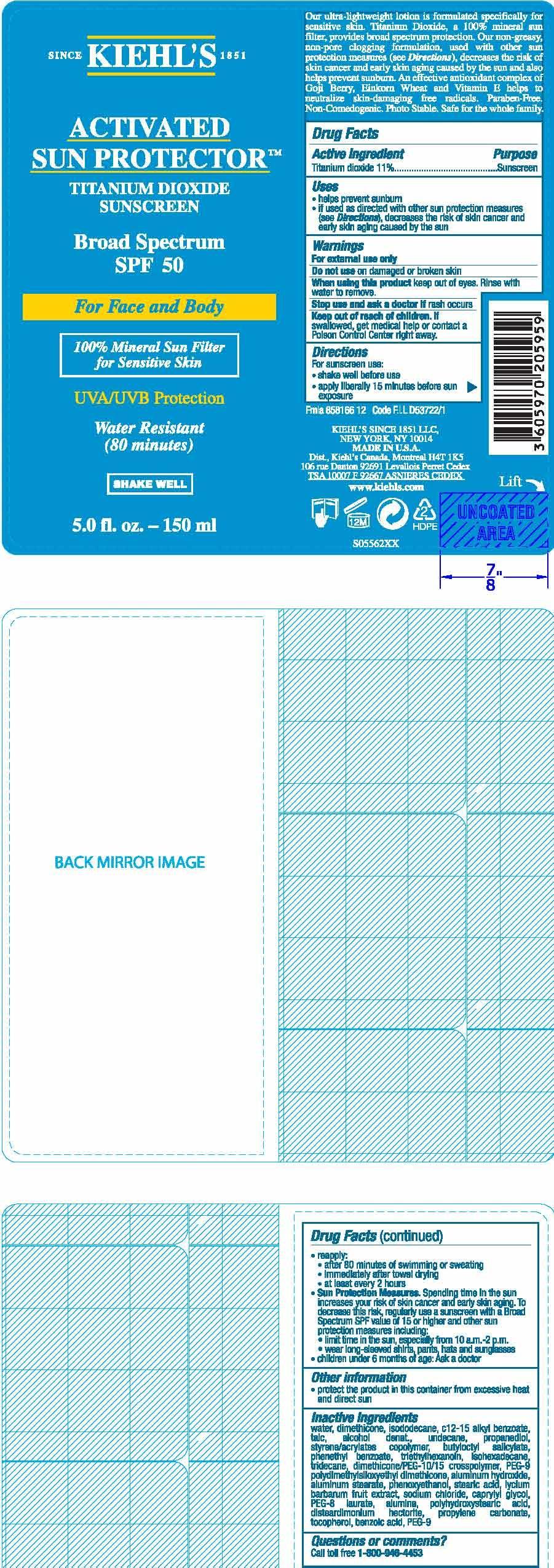 DRUG LABEL: Kiehls Since 1851 Activated Sun Protector For Face and Body Broad Spectrum SPF 50 Sunscreen
NDC: 49967-595 | Form: LOTION
Manufacturer: L'Oreal USA Products Inc
Category: otc | Type: HUMAN OTC DRUG LABEL
Date: 20241227

ACTIVE INGREDIENTS: TITANIUM DIOXIDE 110 mg/1 mL
INACTIVE INGREDIENTS: WATER; DIMETHICONE; ISODODECANE

Drug Facts

Active ingredient

Titanium dioxide 11%

Purpose

Sunscreen

INDICATIONS AND USAGE

- helps prevent sunburn

- if used as directed with other sun protection measures (see Directions), decreases the risk of skin cancer and early skin aging caused by the sun

Warnings

For external use only

Do not use

on damaged or broken skin

When using this product

keep out of eyes. Rinse with water to remove.

Stop use and ask a doctor if

rash occurs

Keep out of reach of children.

If swallowed, get medical help or contact a Poison Control Center right away.

Directions

For sunscreen use:

● shake well before use

● apply liberally 15 minutes before sun exposure

● reapply:

● after 80 minutes of swimming or sweating

● immediately after towel drying

● at least every 2 hours

● Sun Protection Measures. Spending time in the sun increases your risk of skin cancer and early skin aging. To decrease this risk, regularly use asunscreen with a Broad Spectrum SPF value of 15 or higher and other sun protection measures including:

● limit time in the sun, especially from 10 a.m. – 2 p.m.

● wear long-sleeved shirts, pants, hats, and sunglasses

● children under 6 months of age: Ask a doctor

Other information

protect the product in this container from excessive heat and direct sun

Inactive ingredients

water, dimethicone, isododecane, c12-15 alkyl benzoate, talc, alcohol denat., undecane, propanediol, styrene/acrylates copolymer, butyloctyl salicylate, phenethyl benzoate, triethylhexanoin, isohexadecane, tridecane, dimethicone/PEG-10/15 crosspolymer, PEG-9 polydimethylsiloxyethyl dimethicone, aluminum hydroxide, aluminum stearate, phenoxyethanol, stearic acid, lycium barbarum fruit extract, sodium chloride, caprylyl glycol, PEG-8 laurate, alumina, polyhydroxystearic acid, disteardimonium hectorite, propylene carbonate, tocopherol, benzoic acid, PEG-9

Questions or comments?

Call toll free 1-800-946-4453